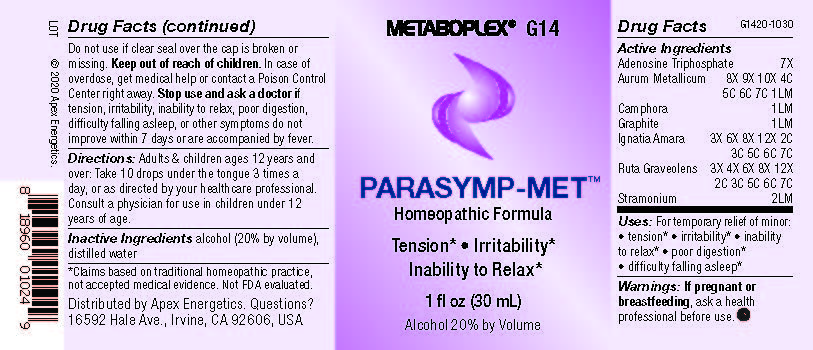 DRUG LABEL: G14
NDC: 63479-0714 | Form: SOLUTION/ DROPS
Manufacturer: Apex Energetics Inc.
Category: homeopathic | Type: HUMAN OTC DRUG LABEL
Date: 20240108

ACTIVE INGREDIENTS: CAMPHOR (NATURAL) 1 [hp_Q]/1 mL; GRAPHITE 1 [hp_Q]/1 mL; STRYCHNOS IGNATII SEED 7 [hp_C]/1 mL; DATURA STRAMONIUM 2 [hp_Q]/1 mL; RUTA GRAVEOLENS FLOWERING TOP 7 [hp_C]/1 mL; ADENOSINE TRIPHOSPHATE 7 [hp_X]/1 mL; GOLD 1 [hp_Q]/1 mL
INACTIVE INGREDIENTS: WATER; ALCOHOL

G14

Active Ingredients
Adenosine Triphosphate | 7X
Aurum Metallicum | 8X 9X 10X 4C 5C 6C 7C 1LM
Camphora | 1LM
Graphite | 1LM
Ignatia Amara | 3X 6X 8X 12X 2C 3C 5C 6C 7C
Ruta Graveolens | 3X 4X 6X 8X 12X 2C 3C 5C 6C 7C
Stramonium | 2LM

INDICATIONS AND USAGE

Uses:

For temporary relief of minor:

tension*

irritability*

inability to relax*

poor digestion*

difficulty falling asleep*

*Claims based on traditional homeopathic practice, not accepted medical evidence. Not FDA evaluated.

Warnings:

PREGNANCY OR BREAST FEEDING

If pregnant or breastfeeding, ask a health professional before use.

Do not use if clear seal over the cap is broken or missing.

Keep out of reach of children. In case of overdose, get medical help or contact a Poison Control Center right away.

Stop use and ask a doctor if tension, irritability, inability to relax, poor digestion, difficulty falling asleep, or other symptoms do not improve within 7 days or are accompanied by fever.

Directions:

Adults & children ages 12 years and over: Take 10 drops under the tongue 3 times a day, or as directed by your healthcare professional. Consult a physician for use in children under 12 years of age.

Inactive Ingredients

alcohol (20% by volume), distilled water

Distributed by Apex Energetics. Questions?

16592 Hale Ave., Irvine, CA 92606, USA

PACKAGE LABEL

METABOPLEX® G14

PARASYMP-MET™

Homeopathic Formula

Tension* Irritability*

Inability to Relax*

1 fl oz (30 mL)

Alcohol 20% by Volume